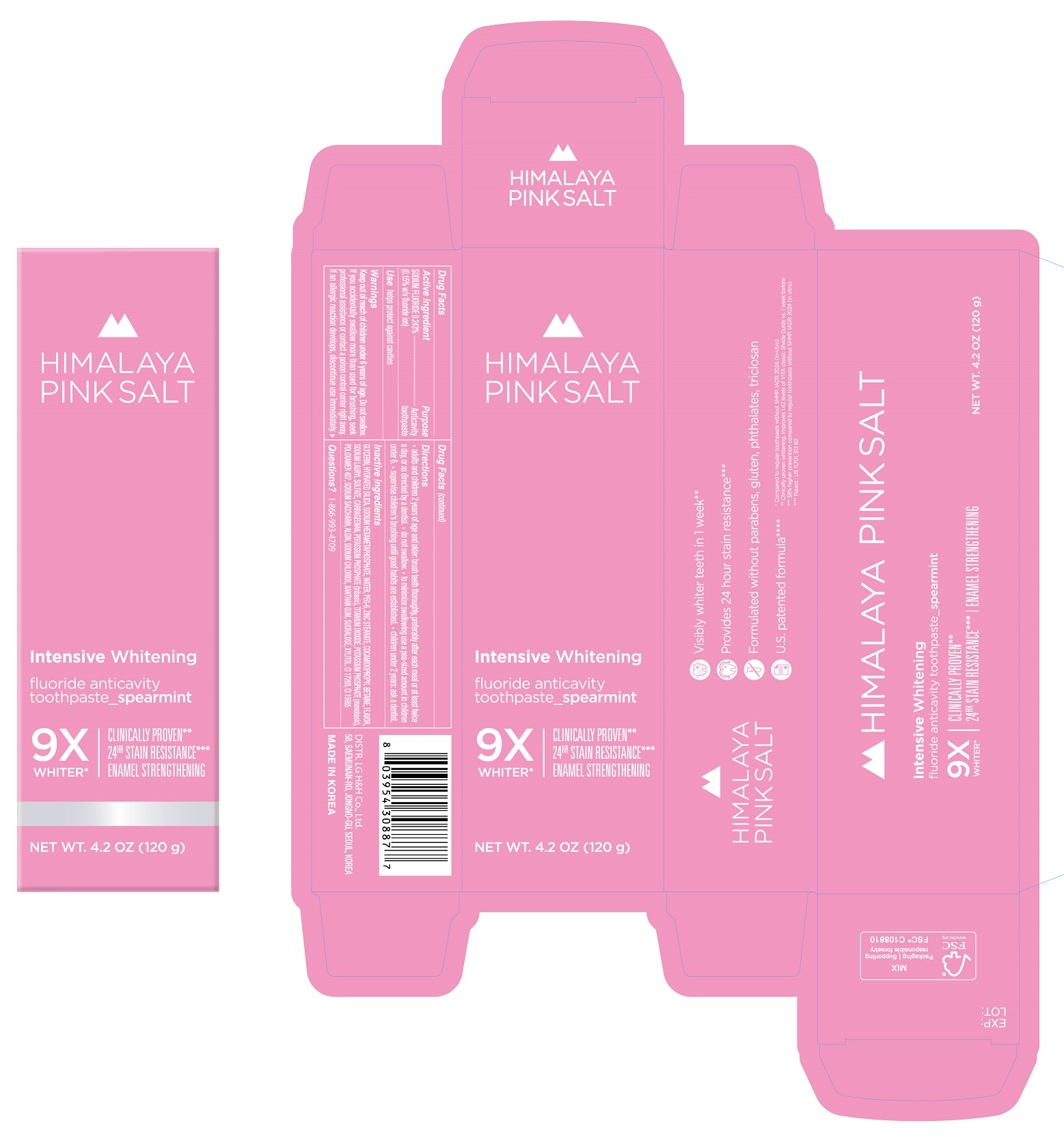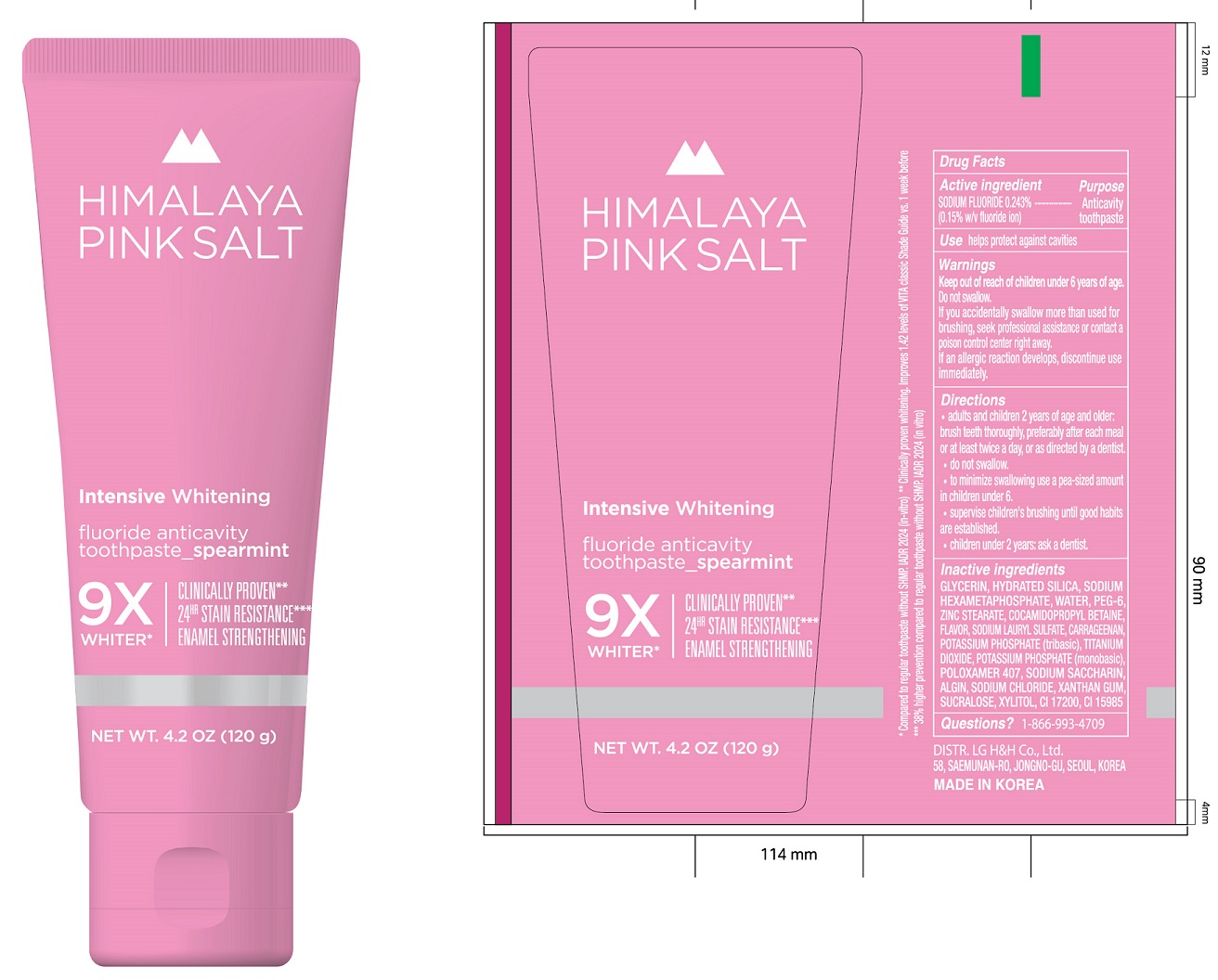 DRUG LABEL: HIMALAYA PINK SALT Intensive Whitening Spearmint
NDC: 53208-591 | Form: PASTE, DENTIFRICE
Manufacturer: LG H&H Co.,Ltd.
Category: otc | Type: HUMAN OTC DRUG LABEL
Date: 20240329

ACTIVE INGREDIENTS: SODIUM FLUORIDE 1.5 mg/1 g
INACTIVE INGREDIENTS: POTASSIUM PHOSPHATE, TRIBASIC; GLYCERIN; COCAMIDOPROPYL BETAINE; WATER; SACCHARIN SODIUM; XYLITOL; FD&C YELLOW NO. 6; SODIUM ALGINATE; SODIUM CHLORIDE; POLYETHYLENE GLYCOL 300; ZINC STEARATE; HYDRATED SILICA; SODIUM POLYMETAPHOSPHATE; SODIUM LAURYL SULFATE; CARRAGEENAN; TITANIUM DIOXIDE; D&C RED NO. 33; MONOPOTASSIUM PHOSPHITE; XANTHAN GUM; SUCRALOSE; POLOXAMER 407

HIMALAYA PINK SALT Intensive Whitening fluoride anticavity toothpaste_spearmint 120g

Active ingredient

SODIUM FLUORIDE 0.243%
(0.15% w/v fluoride ion)

Purpose

Anticavity
toopaste

Use

helps protect against cavities

Warnings

Keep out of reach of children under 6 years of age. Do not swallow.
If you accidentally swallow more than used for brushing, seek professional assistance or contact a poison control center right away.
If an allergic reaction develops, discontinue use immediately

Directions

- adults and children 2 years of age and and older: brush teeth thoroughly, preferably after each meal or at least twice a day, or as directed by a dentist.
- do not swallow.
- to minimize swallowing use a pea-sized amount in children under 6.
- supervise children's brushing until good habits are established.
- children under 2 years: ask a dentist.

Inactive ingredients

GLYCERIN, HYDRATED SILICA, SODIUM HEXAMETAPHOSPHATE, WATER, PEG-6, ZINC STEARATE, COCAMIDOPROPYL BETAINE, FLAVOR, SODIUM LAURYL SULFATE, CARRAGEENAN, POTASSIUM PHOSPHATE (tribasic), TITANIUM DIOXIDE, POTASSIUM PHOSPHATE (monobasic), POLOXAMER 407, SODIUM SACCHARIN, ALGIN, SODIUM CHLORIDE, XANTHAN GUM, SUCRALOSE, XYLITOL, CI 17200, CI 15985

Questions?

1-86-993-4709

DISTR. LG H&H Co., Ltd.
58, SAEMUNAN-RO, JONGNO-GU, SEOUL, KOREA
MADE IN KOREA

- Visibly whiter teeth in 1 week**
- Provides 24 hour stain resistance***
- Formulated without parabens, gluten, phthalates, triclosan
- U.S. patented formula***

* Compared to regular toothpaste without SHMP.IADR2024 (in-vitro)
** Clinically proven whitening. Improves 1.42 levels of VITA classic Shade Guide vs. 1 week before
*** 38% higher prevention compared to regular toothpaste without SHMP.IADR2024 (in-vitro)
**** Patent : US 11,701, 313 B2

Principal Display Panel:

HIMALAYA
PINK SALT
Intensive Whitening
fluoride anticavity
toothpaste_ spearmint
9X
WHITER*

CLINICALLY PROVEN**
24HR STAIN RESISTANCE***
ENAMEL STRENGTHENING

NET WT. 4.2 OZ (120 g)